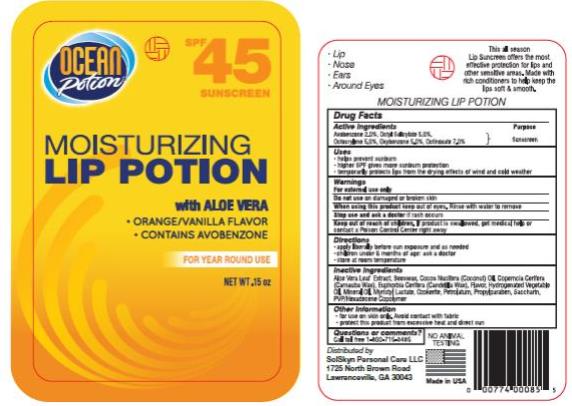 DRUG LABEL: OP spf45 Lip Potion Clear Zinc
NDC: 70281-202 | Form: STICK
Manufacturer: SolSkyn Personal Care LLC
Category: otc | Type: HUMAN OTC DRUG LABEL
Date: 20170201

ACTIVE INGREDIENTS: AVOBENZONE 2 g/100 g; OCTISALATE 5 g/100 g; OCTOCRYLENE 5 g/100 g; OXYBENZONE 5 g/100 g; OCTINOXATE 7 g/100 g
INACTIVE INGREDIENTS: ALOE VERA LEAF; YELLOW WAX; COCONUT OIL; CARNAUBA WAX; CANDELILLA WAX; CORN OIL; MINERAL OIL; MYRISTYL LACTATE; CERESIN; PETROLATUM; PROPYLPARABEN; SACCHARIN; COPOVIDONE

OP Lip SPF45

OP spf45 1oz Lip Potion Clear Zinc

Active Ingredients

Avobenzone 2.0%

Active Ingredients

Octyl Salicylate 5.0%

Active Ingredients

Octocrylene 5.0%

Active Ingredients

Oxybenzone 5.0%

Active Ingredients

Octinoxate 7.0%

Purpose

Sunscreen

Uses:

• Helps prevent sunburn.

• Higher SPF gives more sunburn protection.

• Temporarily protects lips from the drying effects of wind and cold weather.

Warnings:

For external use only

Keep out of reach of children.

If accidentally swallowed, contact a Poison Control Center right away.

Directions:

• Apply liberally before sun exposure as needed.

• Children under 6 months of age: ask a doctor.

• Store at room temperature.

Inactive Ingredients:

Aloe Vera Leaf Extract, Beeswas, Cocos Nucifera (Coconut Oil), Copernica Cerifera (Carnuba Wax), Euphoria Cerifera (Candelilla Wax), Flavor, Hydrogenated Vegetable Oil, Mineral Oil, Myristyl Lactate, Ozokerite, Petrolatum, Propylparaben, Saccharin, PVP/Hexadecene Copolymer

Other information:

• For use on skin only. Avoid contact with fabric.

• Protect this product from excessive heat and direct sun.

Questions or comments?

Call toll free 1-800-715-3485

PRINCIPAL DISPLAY PANEL

Moisturizing
Lip Potion
with Aloe Vera
NET WT .15 oz